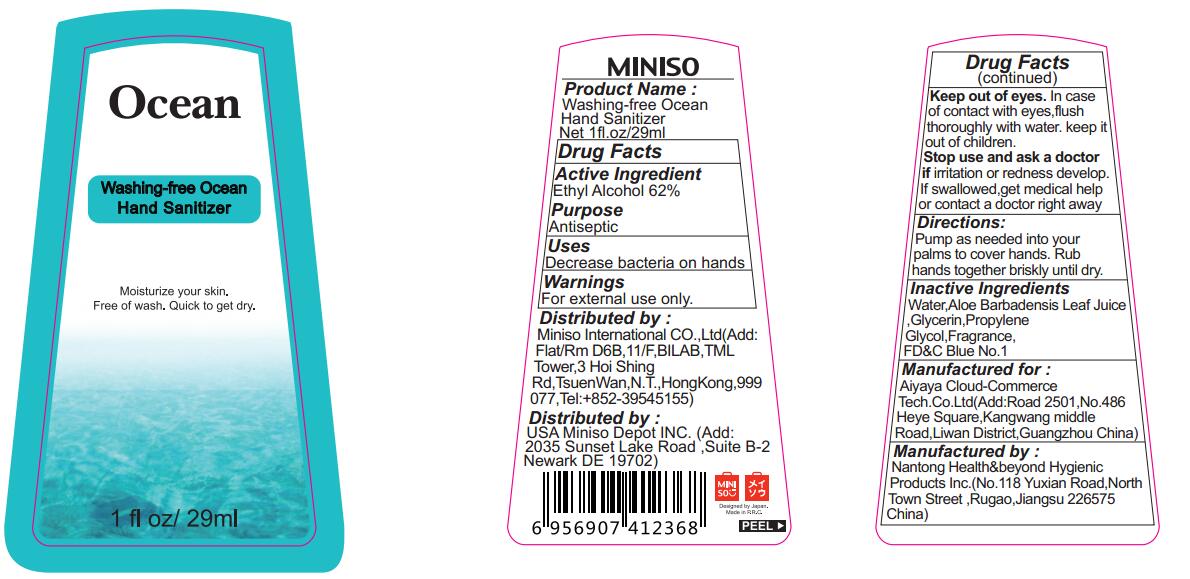 DRUG LABEL: Hand Sanitizer
NDC: 71063-001 | Form: GEL
Manufacturer: Aiyaya Cloud-Commerce Tech Co., Ltd
Category: otc | Type: HUMAN OTC DRUG LABEL
Date: 20161102

ACTIVE INGREDIENTS: ALCOHOL 62 mL/100 mL
INACTIVE INGREDIENTS: WATER; ALOE VERA LEAF; GLYCERIN; PROPYLENE GLYCOL; FD&C BLUE NO. 1

Active Ingredient
Ethyl Alcohol 62%

Purpose
Antiseptic

Warnings

For external use only.

Keep out of eyes. In case of contact with eyes, flush thoroughly with water.

Stop use and ask a doctor if irritation or redness develops. If swallowed, get medical help or contact a doctor right away.

Keep it out of children.

Directions:

Pump as needed into your palms to cover hands. Rub hands together briskly until dry.

Inactive Ingredients

Water, Aloe Barbadenis Leaf Juice, Glycerin, Propylene Glycol, Fragrance, FD&C Blue No.1

Uses

Decrease bacteria on hands